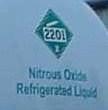 DRUG LABEL: Nitrous Oxide
NDC: 54260-011 | Form: GAS
Manufacturer: Nitrous Oxide
Category: animal | Type: PRESCRIPTION ANIMAL DRUG LABEL
Date: 20251111

ACTIVE INGREDIENTS: Nitrous Oxide 990 mL/1 L

nitrous oxide

PACKAGE LABEL

Airgas

2201

Nitrous Oxide

Refrigerated Liquid